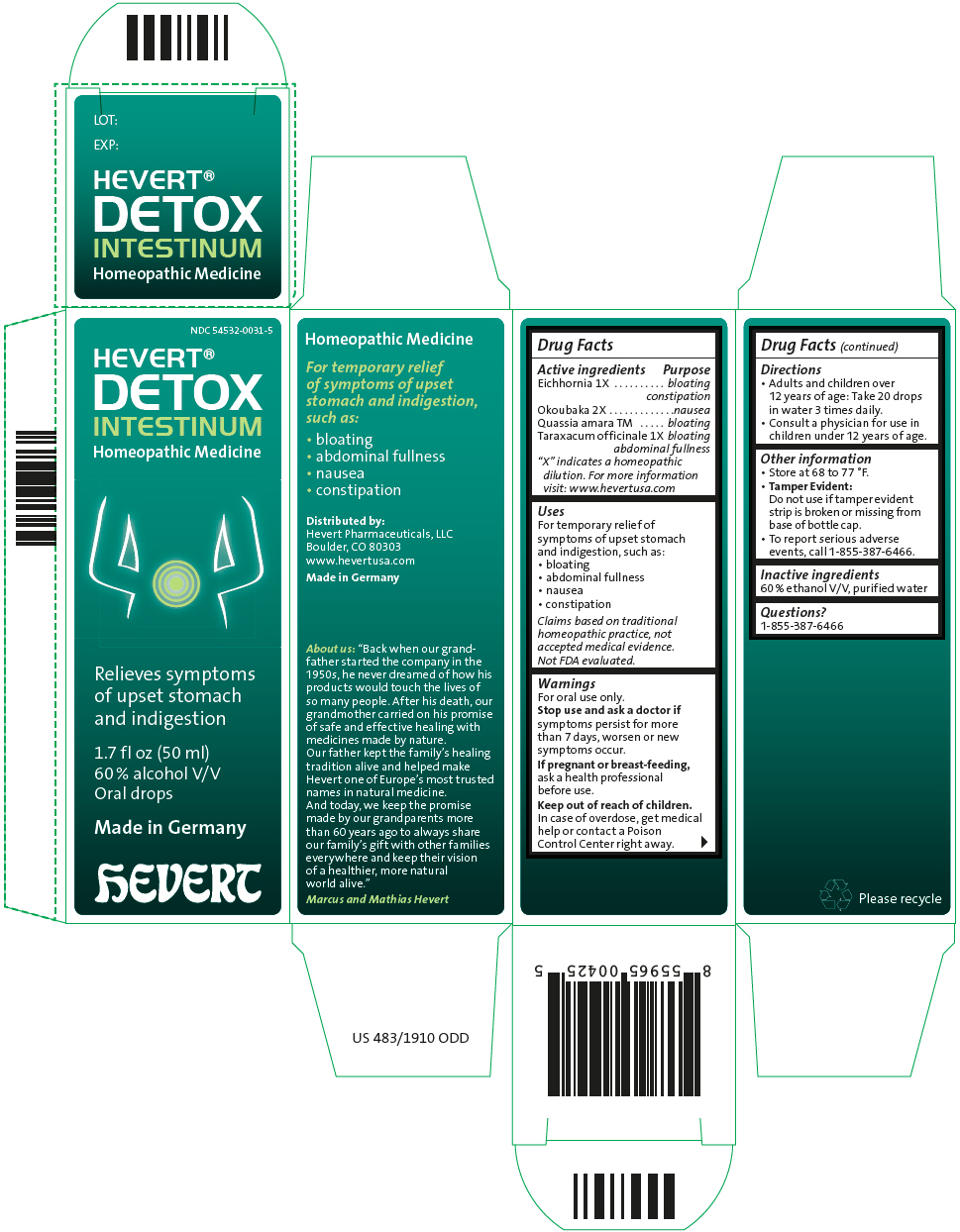 DRUG LABEL: Hevert Detox Intestinum
NDC: 54532-0031 | Form: LIQUID
Manufacturer: Hevert Arzneimittel GmbH & Co KG
Category: homeopathic | Type: HUMAN OTC DRUG LABEL
Date: 20221130

ACTIVE INGREDIENTS: Eichhornia Crassipes Whole 1 [hp_X]/50 mL; OKOUBAKA AUBREVILLEI BARK 2 [hp_X]/50 mL; QUASSIA AMARA WOOD 1 [hp_X]/50 mL; TARAXACUM OFFICINALE 1 [hp_X]/50 mL
INACTIVE INGREDIENTS: ALCOHOL; WATER

Hevert® Detox Intestinum

Drug Facts

ACTIVE INGREDIENT

Active ingredients | Purpose
Eichhornia 1X | bloating constipation
Okoubaka 2X | nausea
Quassia amara TM | bloating
Taraxacum officinale 1X | bloating abdominal fullness
"X" indicates a homeopathic dilution. For more information visit: www.hevertusa.com

Uses

For temporary relief of symptoms of upset stomach and indigestion, such as:

- bloating
- abdominal fullness
- nausea
- constipation

Claims based on traditional homeopathic practice, not accepted medical evidence. Not FDA evaluated.

Warnings

For oral use only.

Stop use and ask a doctor if symptoms persist for more than 7 days, worsen or new symptoms occur.

PREGNANCY OR BREAST FEEDING

If pregnant or breast-feeding, ask a health professional before use.

Keep out of reach of children. In case of overdose, get medical help or contact a Poison Control Center right away.

Directions

- Adults and children over 12 years of age: Take 20 drops in water 3 times daily.
- Consult a physician for use in children under 12 years of age.

Other information

- Store at 68 to 77 °F.
- Tamper Evident:
  Do not use if tamper evident strip is broken or missing from base of bottle cap.
- To report serious adverse events, call 1-855-387-6466.

Inactive ingredients

60 % ethanol V/V, purified water

Questions?

1-855-387-6466

Distributed by:
Hevert Pharmaceuticals, LLC
Boulder, CO 80303

PRINCIPAL DISPLAY PANEL - 50 ml Bottle Carton

NDC 54532-0031-5

HEVERT®
DETOX
INTESTINUM
Homeopathic Medicine

Relieves symptoms
of upset stomach
and indigestion

1.7 fl oz (50 ml)
60 % alcohol V/V
Oral drops

Made in Germany

hEVERT